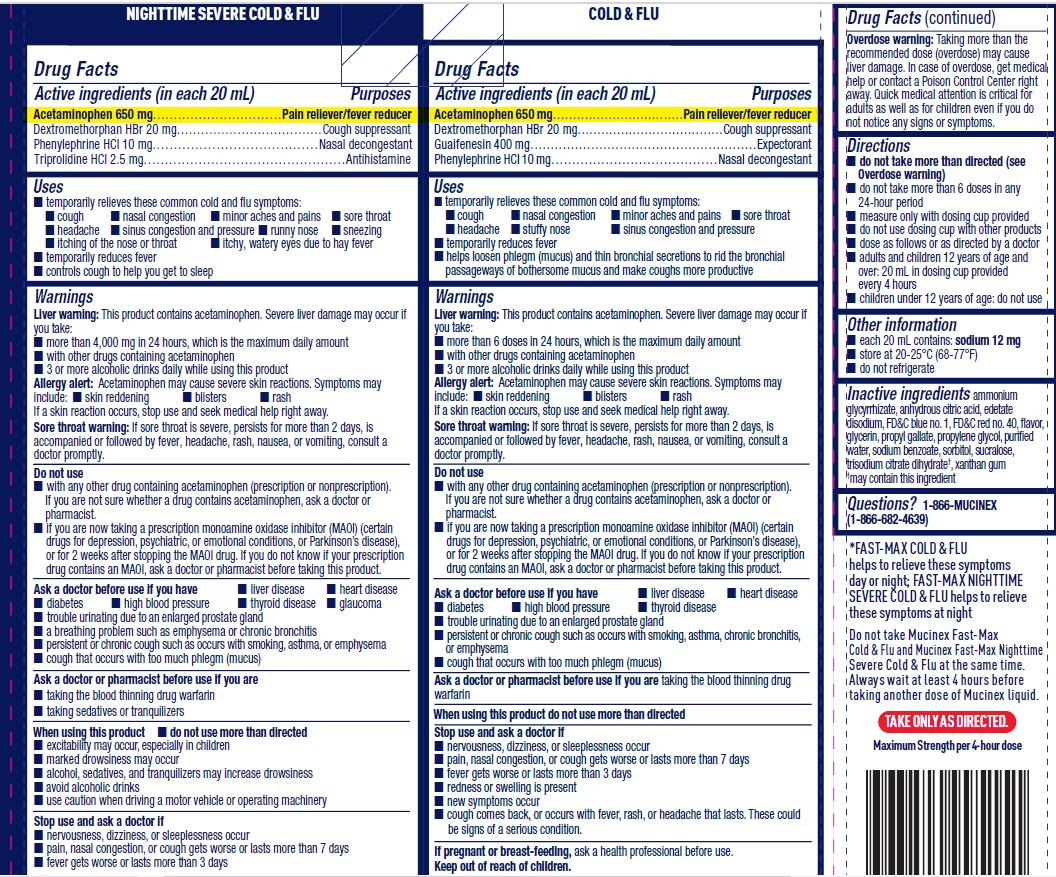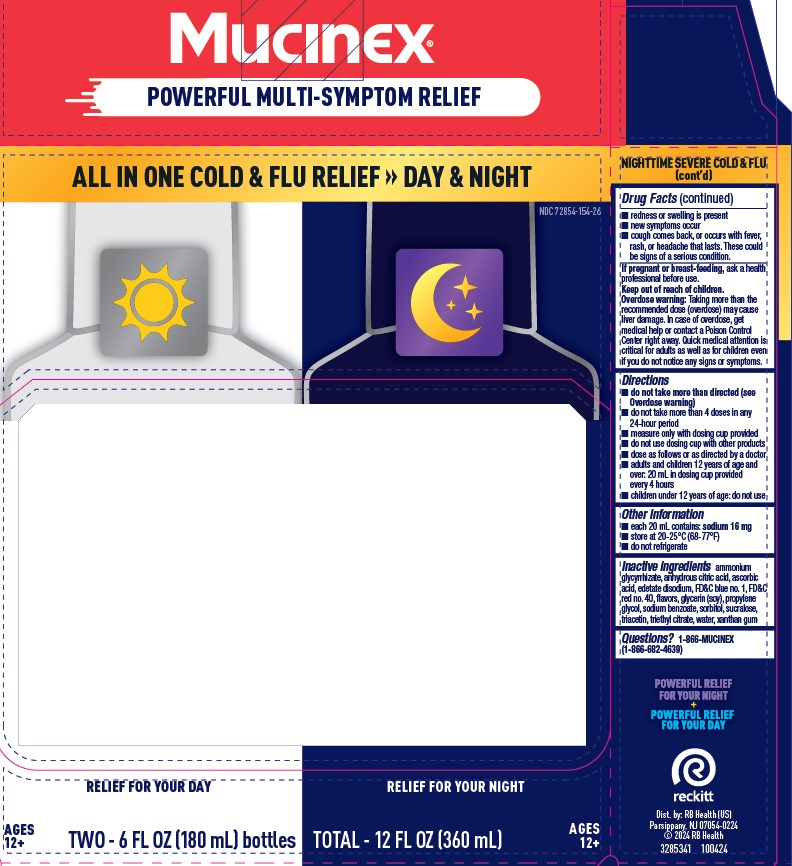 DRUG LABEL: Mucinex Fast-Max Cold and Flu and Mucinex Nighttime Cold and Flu
NDC: 72854-154 | Form: KIT | Route: ORAL
Manufacturer: RB Health (US) LLC
Category: otc | Type: HUMAN OTC DRUG LABEL
Date: 20250805

ACTIVE INGREDIENTS: ACETAMINOPHEN 650 mg/20 mL; DEXTROMETHORPHAN HYDROBROMIDE 20 mg/20 mL; PHENYLEPHRINE HYDROCHLORIDE 10 mg/20 mL; TRIPROLIDINE HYDROCHLORIDE 2.5 mg/20 mL; ACETAMINOPHEN 650 mg/20 mL; DEXTROMETHORPHAN HYDROBROMIDE 20 mg/20 mL; GUAIFENESIN 400 mg/20 mL; PHENYLEPHRINE HYDROCHLORIDE 10 mg/20 mL
INACTIVE INGREDIENTS: GLYCERIN; AMMONIUM GLYCYRRHIZATE; ANHYDROUS CITRIC ACID; ASCORBIC ACID; EDETATE DISODIUM; FD&C BLUE NO. 1; FD&C RED NO. 40; PROPYLENE GLYCOL; SODIUM BENZOATE; SORBITOL; SUCRALOSE; TRIACETIN; TRIETHYL CITRATE; WATER; XANTHAN GUM; AMMONIUM GLYCYRRHIZATE; ANHYDROUS CITRIC ACID; EDETATE DISODIUM; FD&C BLUE NO. 1; FD&C RED NO. 40; GLYCERIN; PROPYL GALLATE; PROPYLENE GLYCOL; WATER; SODIUM BENZOATE; SORBITOL; SUCRALOSE; TRISODIUM CITRATE DIHYDRATE; XANTHAN GUM

Maximum Strength Mucinex® Fast-Max® Cold & Flu and Mucinex® NightShift Severe Cold & Flu

Drug Facts

ACTIVE INGREDIENT

PURPOSE

Active ingredients (in each 20 mL) MUCINEX FAST-MAX COLD & FLU | Purposes
Acetaminophen 650 mg | Pain reliever/fever reducer
Dextromethorphan HBr 20 mg | Cough suppressant
Guaifenesin 400 mg | Expectorant
Phenylephrine HCl 10 mg | Nasal decongestant

Active ingredients (in each 20 mL) MUCINEX NIGHTSHIFT SEVERE COLD & FLU | Purposes
Acetaminophen 650 mg | Pain reliever/fever reducer
Dextromethorphan HBr 20 mg | Cough suppressant
Phenylephrine HCl 10 mg | Nasal decongestant
Triprolidine HCl 2.5 mg | Antihistamine

Uses

MUCINEX FAST-MAX COLD & FLU

- temporarily relieves these common cold and flu symptoms:
  - cough
  - nasal congestion
  - minor aches and pains
  - sore throat
  - headache
  - stuffy nose
  - sinus congestion and pressure
- temporarily reduces fever
- helps loosen phlegm (mucus) and thin bronchial secretions to rid the bronchial passageways of bothersome mucus and make coughs more productive

MUCINEX NIGHTSHIFT SEVERE COLD & FLU

- temporarily relieves these common cold and flu symptoms:
  - cough
  - nasal congestion
  - minor aches and pains
  - sore throat
  - headache
  - sneezing
  - sinus congestion and pressure
  - runny nose
  - itching of the nose or throat
  - itchy, watery eyes due to hay fever
- temporarily reduces fever
- controls cough to help you get to sleep

Warnings

Liver warning

This product contains acetaminophen.

Severe liver damage may occur if you take:

- more than 4000 mg in 24 hours, which is the maximum daily amount
- with other drugs containing acetaminophen
- 3 or more alcoholic drinks daily while using this product

Allergy alert

Acetaminophen may cause severe skin reactions.

Symptoms may include:

- skin reddening
- blisters
- rash

If a skin reaction occurs, stop use and seek medical help right away.

Sore throat warning

If sore throat is severe, persists for more than 2 days, is accompanied or followed by fever, headache, rash, nausea, or vomiting, consult a doctor promptly.

Do not use

- with any other drug containing acetaminophen (prescription or nonprescription). If you are not sure whether a drug contains acetaminophen, ask a doctor or pharmacist.
- if you are now taking a prescription monoamine oxidase inhibitor (MAOI) (certain drugs for depression, psychiatric, or emotional conditions, or Parkinson's disease), or for 2 weeks after stopping the MAOI drug. If you do not know if your prescription drug contains an MAOI, ask a doctor or pharmacist before taking this product.

Ask a doctor before use if you have

- liver disease
- heart disease
- diabetes
- high blood pressure
- thyroid disease
- glaucoma (Nightshift Severe Cold & Flu only)
- trouble urinating due to an enlarged prostate gland
- a breathing problem such as emphysema or chronic bronchitis (Nightshift Severe Cold & Flu only)
- persistent or chronic cough such as occurs with smoking, asthma, chronic bronchitis, or emphysema
- cough that occurs with too much phlegm (mucus)

Ask a doctor or pharmacist before use if you are

- taking the blood thinning drug warfarin
- taking sedatives or tranquilizers (Nightshift Severe Cold & Flu only)

When using this product

- do not use more than directed
- excitability may occur, especially in children (Nightshift Severe Cold & Flu only)
- marked drowsiness may occur (Nightshift Severe Cold & Flu only)
- alcohol, sedatives, and tranquilizers may increase drowsiness (Nightshift Severe Cold & Flu only)
- avoid alcoholic drinks (Nightshift Severe Cold & Flu only)
- use caution when driving a motor vehicle or operating machinery (Nightshift Severe Cold & Flu only)

Stop use and ask a doctor if

- nervousness, dizziness, or sleeplessness occur
- pain, nasal congestion, or cough gets worse or lasts more than 7 days
- fever gets worse or lasts more than 3 days
- redness or swelling is present
- new symptoms occur
- cough comes back, or occurs with fever, rash, or headache that lasts. These could be signs of a serious condition.

PREGNANCY OR BREAST FEEDING

If pregnant or breast-feeding, ask a health professional before use.

Keep out of reach of children.

Overdose warning

Taking more than the recommended dose (overdose) may cause liver damage. In case of overdose, get medical help or contact a Poison Control Center right away. Quick medical attention is critical for adults as well as for children even if you do not notice any signs or symptoms.

Directions

MUCINEX FAST-MAX COLD & FLU

- do not take more than directed (see Overdose warning)
- do not take more than 6 doses in any 24-hour period
- measure only with dosing cup provided
- do not use dosing cup with other products
- dose as follows or as directed by a doctor
- adults and children 12 years of age and over: 20 mL in dosing cup provided every 4 hours
- children under 12 years of age: do not use

MUCINEX NIGHTSHIFT SEVERE COLD & FLU

- do not take more than directed (see Overdose warning)
- do not take more than 4 doses in any 24-hour period
- measure only with dosing cup provided
- do not use dosing cup with other products
- dose as follows or as directed by a doctor
- adults and children 12 years of age and over: 20 mL in dosing cup provided every 4 hours
- children under 12 years of age: do not use

Other information

- each 20 mL contains: sodium 12 mg (Fast-Max Cold & Flu only) and sodium 16 mg (Nightshift Severe Cold & Flu only)
- store at 20-25°C (68-77°F)
- do not refrigerate

Inactive ingredients (MUCINEX FAST-MAX COLD & FLU)

ammonium glycyrrhizate, anhydrous citric acid, edetate
disodium, FD&C blue no. 1, FD&C red no. 40, flavor,
glycerin, propyl gallate, propylene glycol, purified
water, sodium benzoate, sorbitol, sucralose,
trisodium citrate dihydrate†, xanthan gum
†may contain this ingredient

Inactive ingredients (MUCINEX NIGHTSHIFT SEVERE COLD & FLU)

ammonium glycyrrhizate, anhydrous citric acid, ascorbic
acid, edetate disodium, FD&C blue no. 1, FD&C
red no. 40, flavors, glycerin (soy), propylene
glycol, sodium benzoate, sorbitol, sucralose,
triacetin, triethyl citrate, water, xanthan gum

Questions?

1-866-MUCINEX (1-866-682-4639) You may also report side effects to this phone number.

Dist. by: RB Health (US), Parsippany, NJ 07054-0224

PRINCIPAL DISPLAY PANEL - Kit Carton

NDC 72854-154-26

DAY & NIGHT COLD & FLU PACK

Mucinex®
FAST-MAX®

COLD & FLU

Acetaminophen – Pain Reliever/Fever Reducer
Dextromethorphan HBr – Cough Suppressant
Guaifenesin – Expectorant • Phenylephrine HCl – Nasal Decongestant

SORE THROAT
FEVER
HEADACHE
BODY PAIN
ALL IN
ONE*
CHEST CONGESTION
COUGH
NASAL CONGESTION
SINUS CONGESTION
SINUS PRESSURE

FOR
AGES 12+
TWO – 6 FL OZ (180 mL) bottles

MAXIMUM STRENGTH
Mucinex®
NIGHTTIME

COLD & FLU

Acetaminophen – Pain Reliever/Fever Reducer
Dextromethorphan HBr – Cough Suppressant
Phenylephrine HCl – Nasal Decongestant • Triprolidine HCl – Antihistamine

SORE THROAT
FEVER
HEADACHE
BODY PAIN
ALL IN
ONE*
ITCHY THROAT
COUGH
NASAL CONGESTION
SNEEZING
RUNNY NOSE

TOTAL – 12 FL OZ (360 mL)
FOR
AGES 12+